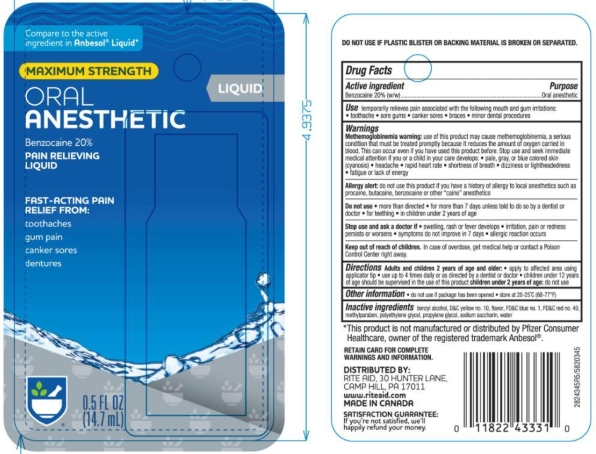 DRUG LABEL: Rite Aid
NDC: 11822-0345 | Form: LIQUID
Manufacturer: Rite Aid
Category: otc | Type: HUMAN OTC DRUG LABEL
Date: 20251113

ACTIVE INGREDIENTS: BENZOCAINE 20 g/100 g
INACTIVE INGREDIENTS: POLYETHYLENE GLYCOL 400; PROPYLENE GLYCOL; SACCHARIN SODIUM; METHYLPARABEN; BENZYL ALCOHOL; FD&C RED NO. 40; D&C YELLOW NO. 10; FD&C BLUE NO. 1; WATER

5820345 Rite Aid Max Str Oral Pain Relief

Active ingredient

Benzocaine 20% (w/w)

Purpose

Oral anesthetic

Use

temporarily relieves pain associated with the following mouth irritations

- toothache
- sore gums
- canker sores
- braces
- minor dental procedures

Warnings

Methemoglobinemia warning: use of this product may cause methemoglobinemia, a serious condition that must be treated promptly because it reduces the amount of oxygen carried in blood. This can occur even if you have used this product before. Stop use and seek immediate medical attention if you or a child in yoru care develops:

- pale, gray, or blue colored skin (cyanosis)
- headache
- rapid heart rate
- shortness of breath
- dizziness or lighteadedness
- fatigue or lack of energy

Allergy alert: do not use this product if you have a history of allergy to local anesthetics such as procaine, butacaine, benzocaine or other “caine” anesthetics

Do not use

- more than directed
- for more than 7 days unless directed by a dentist or doctor
- for teething
- in children under 2 years of age

Stop use and ask a doctor if

- swelling, rash or fever develops
- irritation, pain or redness persists or worsens
- symptoms do not improve in 7 days
- allergic reaction occurs

Keep out of reach of children. In case of overdose, get medical help or contact a Poison Control Center right away.

Directions

Adults and children 2 years of age and older:

- apply to affected area using applicator tip
- use up to 4 times daily or as directed by a dentist or doctor
- children under 12 years of age should be supervised in the use of this product

children under 2 years of age: do not use

Other information

- do not use if package has been opened
- store at 20-25°C (68-77°F)

INACTIVE INGREDIENT

Inactive ingredients Benzyl Alcohol, D&C Yellow 10, FD&C Blue 1, FD&C Red 40, Methylparaben, Natural and Artificial Flavor, Polyethylene Glycol, Propylene Glycol, Sodium Saccharin, Water

DISTRIBUTED BY:

RITE AID, 30 HUNTER LANE

CAMP HILL, PA 17011

MADE IN CANADA